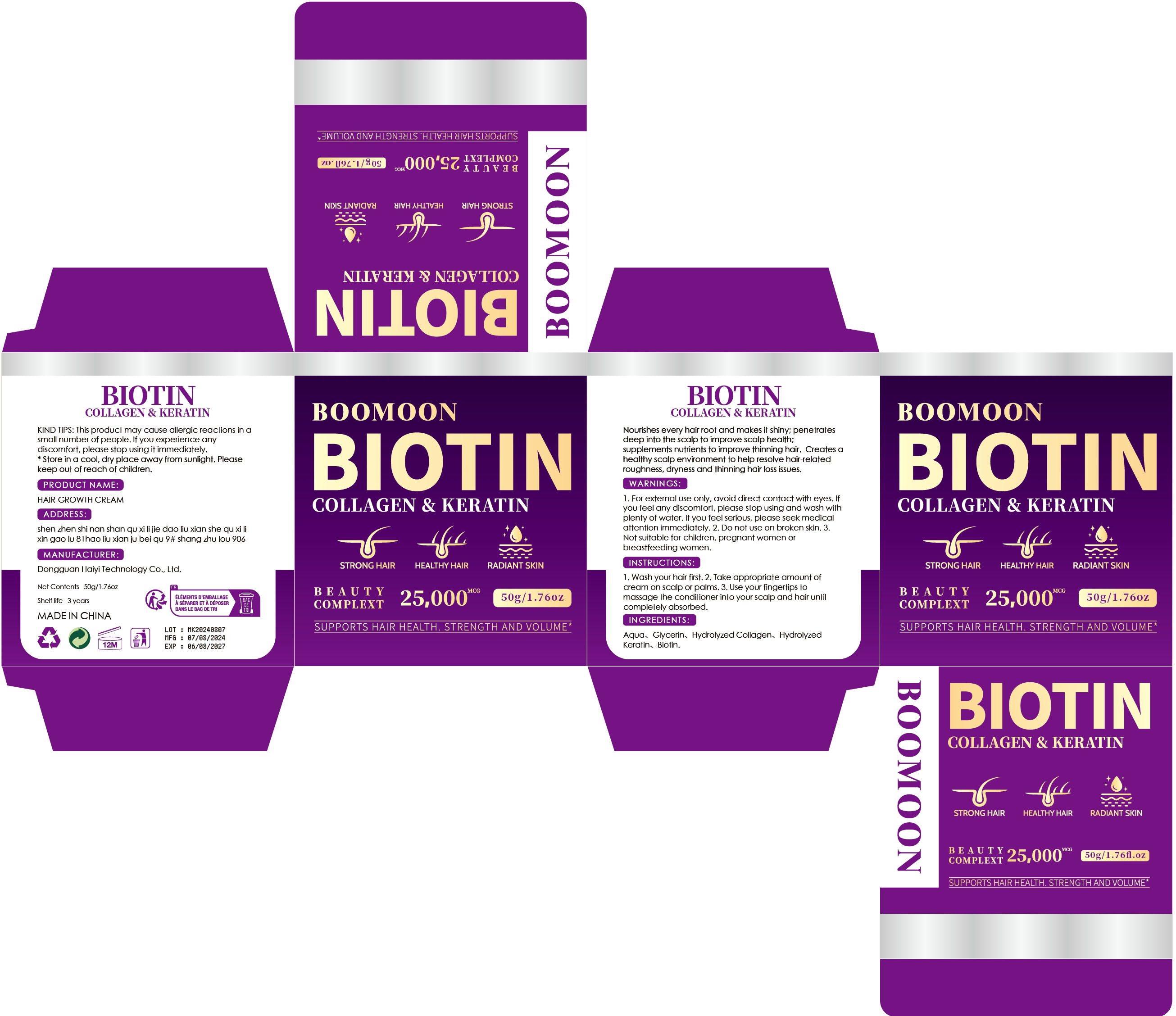 DRUG LABEL: HAIR GROWTH Cream
NDC: 84732-079 | Form: CREAM
Manufacturer: Dongguan Haiyi Technology Co.,Ltd.
Category: otc | Type: HUMAN OTC DRUG LABEL
Date: 20241101

ACTIVE INGREDIENTS: GLYCERIN 1 mg/50 g
INACTIVE INGREDIENTS: COCODIMONIUM HYDROXYPROPYL HYDROLYZED KERATIN (1000 MW); WATER; BIOTIN; COLLAGEN ALPHA-1(I) CHAIN BOVINE

Active ingredien

Glycerin

Inactive ingredient

Aqua、Hydrolyzed Collagen、Hydrolyzed Keratin、Biotin.

Purpose section

Nourishes every hair root and makes it shiny; penetrates deep into the scalp to improve scalp health;supplements nutrients to improve thinning hair. Creates ahealthy scalp environment to help resolve hair-relatedroughness,dryness and thinning hair loss issues.

Warning

1. For external use only, avoid direct contact with eyes. lfyou feel any discomfort, please stop using and wash withplenty of water. lf you feel serious, please seek medicalattention immediately.

2. Do not use on broken skin.

3.Not suitable for children, pregnant women orbreastfeeding women.

stop use

This product may cause allergic reactions in asmall number of people.
lf youexperience any discomfort,please stop using it immediately.

not use

Not suitable for use by children, pregnantor breast feeding people.

OUT OF CHILDREN

KEEP THE PRODUCT OUT OF REACH OF CHILDREN to

HOW TO USE

1. Wash your hair first.

2. Take appropriate amount ofcream on scalp or palms.

3. Use your fingertips tomassage the conditioner into your scalp and hair untilcompletely absorbed.

Dosage

take an appropriateamount,Use 2-3 times a week